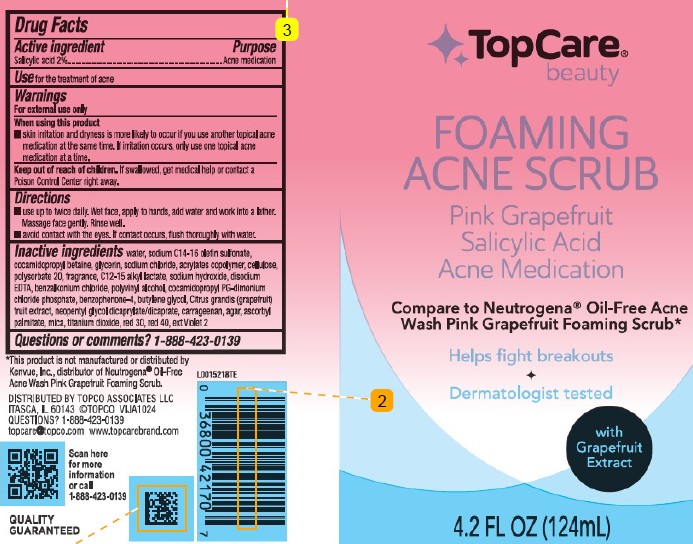 DRUG LABEL: Acne Scrub
NDC: 36800-821 | Form: CREAM
Manufacturer: Topco Associates LLC
Category: otc | Type: HUMAN OTC DRUG LABEL
Date: 20260213

ACTIVE INGREDIENTS: SALICYLIC ACID 20 mg/1 mL
INACTIVE INGREDIENTS: WATER; SODIUM C14-16 OLEFIN SULFONATE; COCAMIDOPROPYL BETAINE; GLYCERIN; SODIUM CHLORIDE; BUTYL ACRYLATE/METHYL METHACRYLATE/METHACRYLIC ACID COPOLYMER (18000 MW); POWDERED CELLULOSE; POLYSORBATE 20; C12-15 ALKYL LACTATE; SODIUM HYDROXIDE; EDETATE DISODIUM; BENZALKONIUM CHLORIDE; POLYVINYL ALCOHOL, UNSPECIFIED; COCAMIDOPROPYL PROPYLENE GLYCOL-DIMONIUM CHLORIDE PHOSPHATE; SULISOBENZONE; BUTYLENE GLYCOL; PUMMELO; NEOPENTYL GLYCOL DICAPRYLATE/DICAPRATE; CARRAGEENAN; AGAR; ASCORBYL PALMITATE; MICA; TITANIUM DIOXIDE; D&C RED NO. 30; FD&C RED NO. 40; EXT. D&C VIOLET NO. 2

Top Care 821.004/821AH
Acne Scrub Pink Grapefruit

Active ingredient

Salicylic acid (2%)

Purpose

Acne medication

Use

for the treatment of acne

Warnings

For external use only

When using this product

- Skin irritation and dryness is more likely to occur if you use another topical acne medication at the same time. If irritation occurs, only use one topical acne medication at a time.

Keep out of reach of children

If swallowed, get medical help or contact a Poison control Center right away.

Directions

- use up to twice daily. Wet face, apply to hands, add water and work into a lather. Massage face gently. Rinse well.
- avoid contact with the eyes. If contact occurs, flush thoroughly with water.

Inactive ingredients

water, sodium C14-16 olefin sulfonate, cocamidopropyl betaine, glycerin, sodium chloride, acrylates copolymer, cellulose, polysorbate 20, fragrance, C12-15 alkyl lactate, sodium hydroxide, disodium EDTA, benzalkonium chloride, polyvinyl alcohol, cocamidopropyl PG-dimonium chloride phosphate, benzophenone-4, butylene glycol, Citrus grandis (grapefruit) fruit extract, neopentyl glycol dicaprylate/dicaprate, carrageenan, agar, ascorbyl palmitate, mica, titanium dioxide, red 30, red 40, ext Violet 2

Questions or comments?

1-888-423-0139

Disclaimer

*This product is not manufactured or distributed by Kenvue, Inc., disributor of NeutrogenaOil-Free Acne Wash Pink Grapefruit Foaming Scrub.

Adverse Reaction

Distributed by Topco Associates LLC

Itasca, IL 60143 ©TOPCO VIJA1024

Questions? 1-888-423-0139

topcare@topco.comwww.topcarebrand.com

Scan here for more information or call 1-888-423-0139

QUALITY GUARANTEED

principal display panel

TopCare®

beauty

FOAMING

ACNE SCRUB

Pink Grapefruit

Salicylic Acid

Acne Medication

Compare to Neutrogena®Oil-Free Acne Wash Pink Grapefruit Foaming Scrub*

Helps fight breakouts

Dermatologist tested

With Grapefruit Extract

4.2 FL OZ (124 mL)